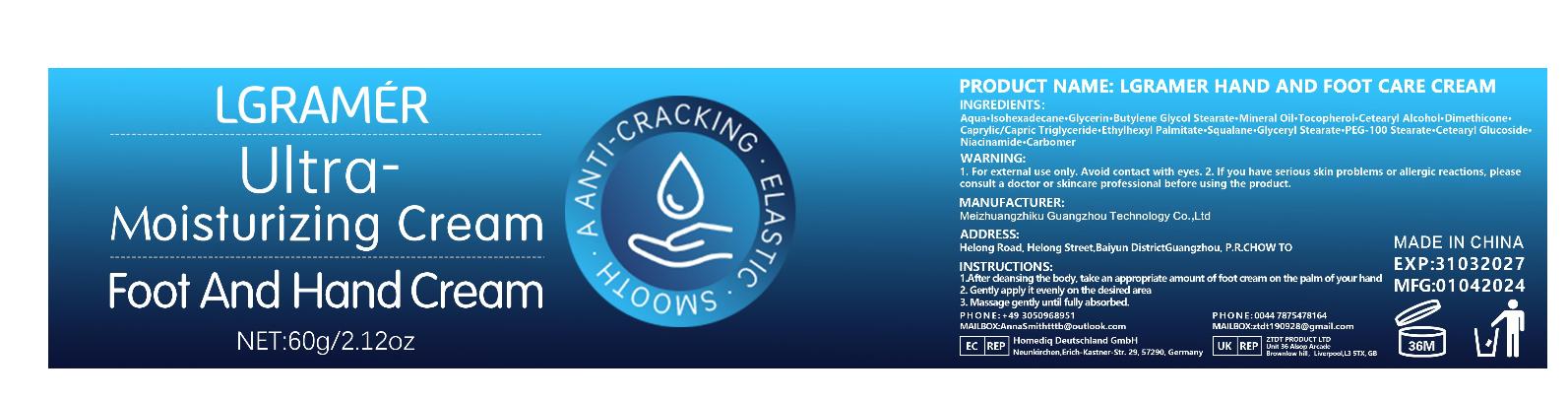 DRUG LABEL: Lgramer Hand and Foot Care Cream
NDC: 84350-002 | Form: CREAM
Manufacturer: Shenzhen Sihai Juntong Technology Co., Ltd
Category: otc | Type: HUMAN OTC DRUG LABEL
Date: 20240613

ACTIVE INGREDIENTS: SQUALANE 1 g/100 mg
INACTIVE INGREDIENTS: WATER

ACTIVE INGREDIENT

Tocopheryl acetate 5%

INACTIVE INGREDIENT

Water 5%

PURPOSE

Moisturizing

Warining

WARNING:1. For external use only. Avoid contact with eyes. 2. lf you have serious skin problems or allergic reactions, pleaseconsult a doctor or skincare professional before using the product.

Do not use

lf you have allergic reactions, stop to use

when using this product

1.After cleansing the body, take an appropriate amount of foot cream on the palm of your hand

2. Gently apply it evenly on the desired area
3. Massage gently until fully absorbed.

Keep out of reach of children

use

INSTRUCTIONS:

1.After cleansing the body, take an appropriate amount of foot cream on the palm of your hand

2. Gently apply it evenly on the desired area

3. Massage gently until fully absorbed.

Dosage and administration

appropriate amount

PRINCIPAL DISPLAY PANEL

60g NDC:84350-002-01